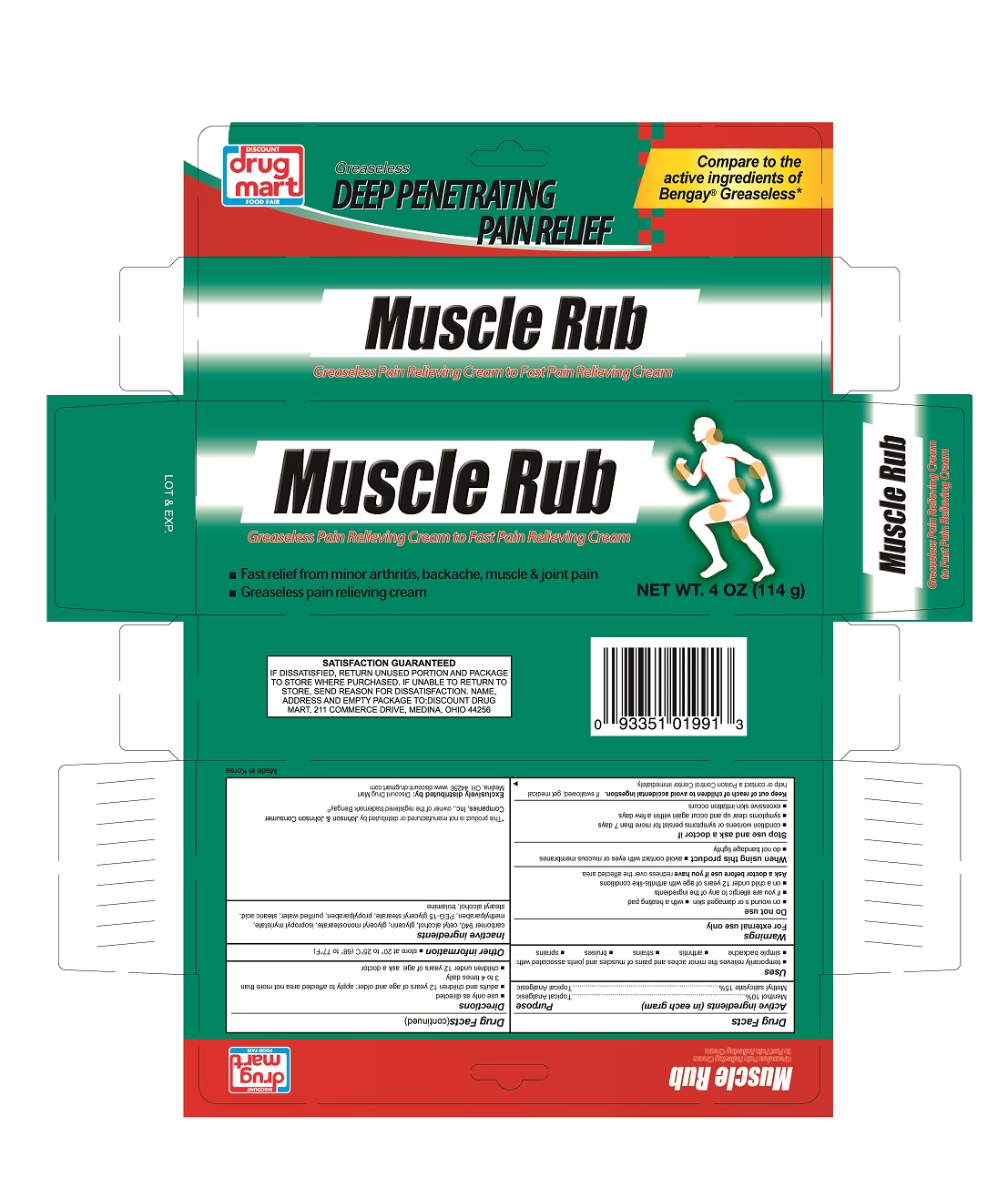 DRUG LABEL: Muscle and Joint Pain Relief
NDC: 53943-991 | Form: CREAM
Manufacturer: Discount Drug Mart, Inc.
Category: otc | Type: HUMAN OTC DRUG LABEL
Date: 20151109

ACTIVE INGREDIENTS: MENTHOL 10 g/100 g; METHYL SALICYLATE 15 g/100 g
INACTIVE INGREDIENTS: CARBOMER HOMOPOLYMER TYPE C; CETYL ALCOHOL; GLYCERIN; GLYCERYL MONOSTEARATE; ISOPROPYL MYRISTATE; METHYLPARABEN; PEG-15 GLYCERYL STEARATE; PROPYLPARABEN; WATER; STEARIC ACID; STEARYL ALCOHOL; TROLAMINE

Drug Facts

Active ingredients

Menthol 10%

Methyl salicylate 15%

Uses

temporarily relieves the minor aches and pains of muscles and joints associated with:

- simple backache
- arthritis
- strains
- bruises
- sprains

Warnings

For external use only

Do not use

- on wounds or damaged skin
- with a heating pad
- If you are allergic any of the ingredients
- on a child under 12 years of age with arthritis-like conditions

Ask a doctor before use if you have

redness over the affected area.

When using this product

- avoid contact with eyes or mucous membranes
- do not bandage tightly

Stop use and ask a doctor if

- condition worsens or symptoms persist for more than 7 days
- symptoms clear up and occur again within a few days
- excessive skin irritation occurs

Keep out of reach of children to avoid accidental ingestion.

If swallowed, get medical help or contact a Poison Control Center immediately.

Directions

- use only as directed
- adults and children 12 years of age and older: apply to affected area not more than 3 to 4 times daily
- children under 12 years of age: ask a doctor

Other information

- store at 20° to 25°C (68° to 77°F)

Inactive ingredients

carbomer 940, cetyl alcohol, glycerin, glycerol monostearate, isoprophyl myristate, methylparaben, PEG 15 glyceryl stearate, propylparaben, purified water, stearic acid, stearyl alcohol, trolamine

Purpose

Topical analgesic

Topical analgesic

Package label

Discount Drug Mart Greaseless Muscle Rub